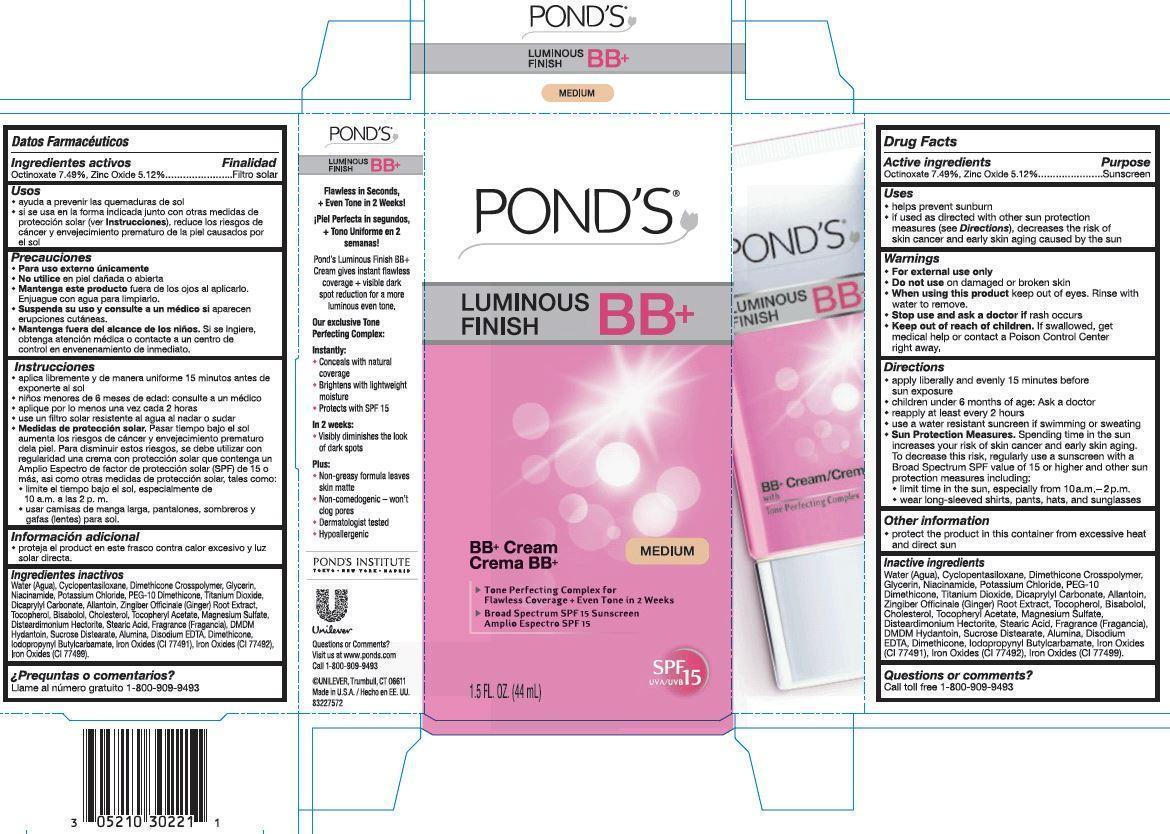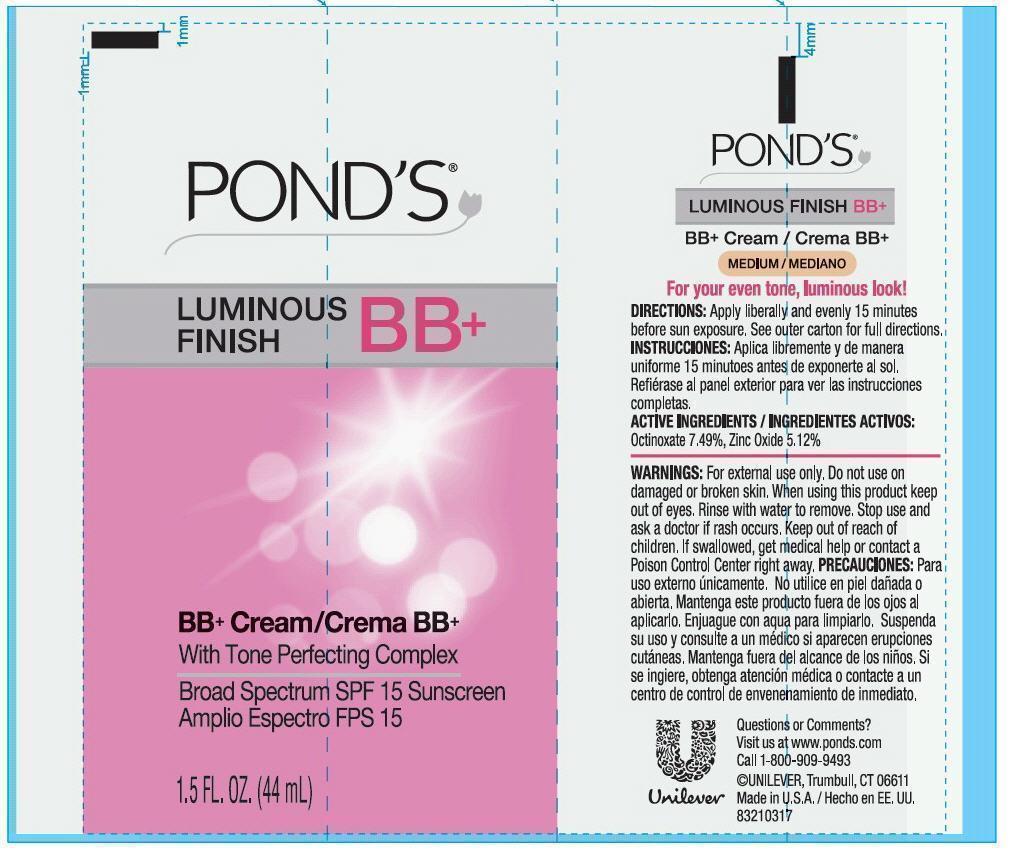 DRUG LABEL: Ponds
NDC: 64942-1284 | Form: LOTION
Manufacturer: CONOPCO Inc. d/b/a Unilever
Category: otc | Type: HUMAN OTC DRUG LABEL
Date: 20141022

ACTIVE INGREDIENTS: OCTINOXATE 7.49 g/100 mL; ZINC OXIDE 5.12 g/100 mL
INACTIVE INGREDIENTS: WATER; CYCLOMETHICONE 5; TITANIUM DIOXIDE; GLYCERIN; NIACINAMIDE; POTASSIUM CHLORIDE; PEG-10 DIMETHICONE (600 CST); DICAPRYLYL CARBONATE; ALLANTOIN; GINGER; TOCOPHEROL; .ALPHA.-BISABOLOL, (+/-)-; CHOLESTEROL; .ALPHA.-TOCOPHEROL ACETATE; MAGNESIUM SULFATE; STEARIC ACID; DMDM HYDANTOIN; SUCROSE DISTEARATE; EDETATE DISODIUM; DIMETHICONE; IODOPROPYNYL BUTYLCARBAMATE; FERRIC OXIDE RED; FERRIC OXIDE YELLOW; FERROSOFERRIC OXIDE

Pond's Luminous Finish BB Cream Medium SPF 15

Active Ingredients
Octinoxate 7.49%, Zinc Oxide 5.12%

Purpose
Sunscreen

Uses

· helps prevent sunburn
· if used as directed with other sun protection measures (see Directions), decreases the risk of skin cancer and early skin aging caused by the sun

Warnings

· For external use only

· Do not use on damaged or broken skin

· When using this product keep out of eyes. Rinse with water to remove.

· Stop use and ask a doctor if rash occurs

· Keep out of reach of children. If swallowed, get medical help or contact a Poison Control Center right away.

Directions

· apply liberally and evenly 15 minutes before sun exposure
· children under 6 months of age: Ask a doctor
· reapply at least every 2 hours
· use a water resistant sunscreen if swimming or sweating
Sun Protection Measures. Spending time in the sun increases your risk of skin cancer and early skin aging. To decrease this risk, regularly use a sunscreen with a Broad Spectrum SPF value of 15 or higher and other sun protection measures including:
· limit time in the sun, especially from 10a.m. - 2p.m.
· wear long-sleeved shirts, pants, hats, and sunglasses

Inactive ingredients

Water (Agua), Cyclopentasiloxane, Glycerin, Niacinamide, Dimethicone Crosspolymer, Potassium Chloride, PEG-10 Dimethicone, Titanium Dioxide, Dicaprylyl Carbonate, Disteardimonium Hectorite, Magnesium Sulfate, Stearic Acid, Cholesterol, Bisabolol, Allantoin, Zingiber Officinale (Ginger) Root Extract, Tocopherol, Tocopheryl Acetate, Fragrance (Fragancia), DMDM Hydantoin, Sucrose Distearate, Alumina, Disodium EDTA, Dimethicone, Iodopropynyl Butylcarbamate, Iron Oxides (CI 77491), Iron Oxides (CI 77492), Iron Oxides (CI 77499).

Questions or comments?
Call toll free 1-800-909-9493